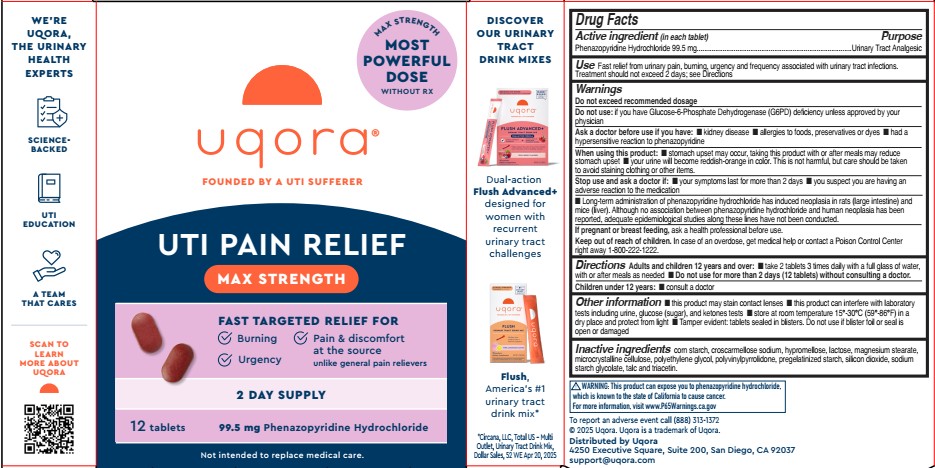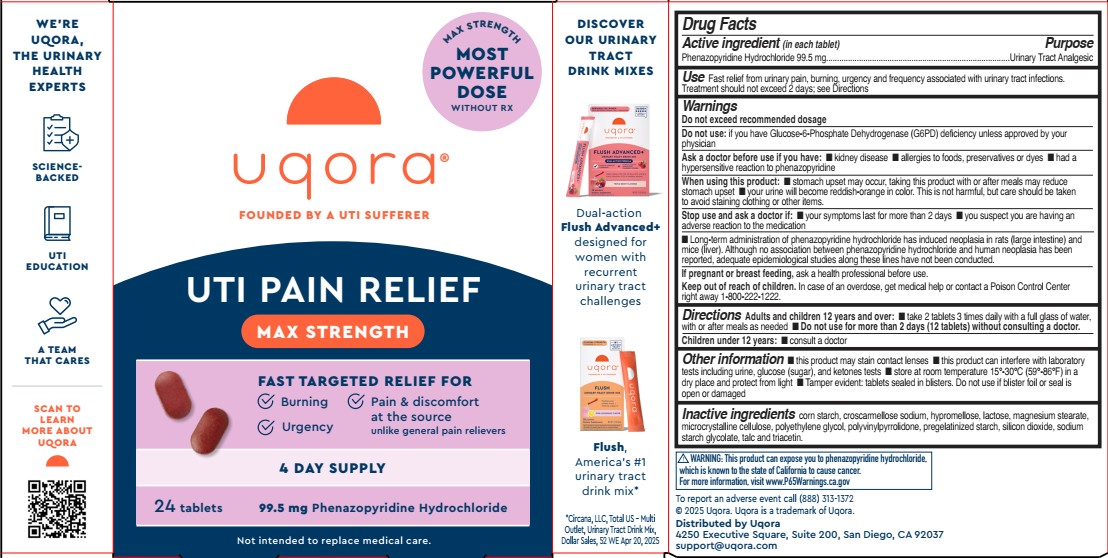 DRUG LABEL: Uqora Maximum UTI Pain Relief
NDC: 73712-114 | Form: TABLET
Manufacturer: Bonafide Health, LLC dba Uqora
Category: otc | Type: HUMAN OTC DRUG LABEL
Date: 20251027

ACTIVE INGREDIENTS: PHENAZOPYRIDINE HYDROCHLORIDE 99.5 mg/1 1
INACTIVE INGREDIENTS: POLYETHYLENE GLYCOL, UNSPECIFIED; STARCH, CORN; SILICON DIOXIDE; CROSCARMELLOSE SODIUM; SODIUM STARCH GLYCOLATE TYPE A; TALC; POVIDONE; HYPROMELLOSE, UNSPECIFIED; MICROCRYSTALLINE CELLULOSE; TRIACETIN; LACTOSE; MAGNESIUM STEARATE

Uqora Maximum UTI Pain Relief

Active ingredient (in each tablet)

Phenazopyridine Hydrochloride 99.5 mg .

Purpose

Urinary Tract Analgesic

Use

Fast relief from urinary pain, burning, urgency and frequency associated with urinary tract infections. Treatment should not exceed 2 days; see Directions.

Warnings

Do not exceed recommended dosage

Do not use: if you have Glucose-6-Phosphate Dehydrogenase (G6PD) deficiency unless approved by your physician.

Ask doctor before use if you have

■ kidney disease
■ allergies to foods, preservatives or dyes
■ had a hypersensitive reaction to phenazopyridine

When using this product

■ stomach upset may occur, taking this product with or after meals may reduce stomach upset
■ your urine will become reddish-orange in color. This is not harmful, but care should be taken to avoid staining clothing or other items.

----

■ Long-term administration of phenazopyridine hydrochloride has induced neoplasia in rats (large intestine) andmice (liver). Although no association between phenazopyridine hydrochloride and human neoplasia has beenreported, adequate epidemiological studies along these lines have not been conducted.

Stop use and ask doctor if

■ your symptoms last for more than 2 days
■ you suspect you are having an adverse reaction to the medication

PREGNANCY OR BREAST FEEDING

If pregnant or breast feeding, ask a health professional before use.

Keep out of reach of children. In case of an overdose, get medical help or contact a Poison Control Center right away 1-800-222-1222.

Directions

Adults and children 12 years and over:
■ take 2 tablets 3 times daily with a full glass of water, with or after meals as needed

■ Do not use for more than 2 days (12 tablets) without consulting a doctor.

Children under 12 years:

■ consult a doctor

Other information

■ this product may stain contact lenses ■ this product can interfere with laboratorytests including urine, glucose (sugar), and ketones tests ■ store at room temperature 15°-30°C (59°-86°F) in adry place and protect from light ■ Tamper evident: tablets sealed in blisters. Do not use if blister foil or seal isopen or damaged

Inactive ingredients

corn starch, croscarmellose sodium, hypromellose, lactose, magnesium stearate,microcrystalline cellulose, polyethylene glycol, polyvinylpyrrolidone, pregelatinized starch, silicon dioxide, sodiumstarch glycolate, talc and triacetin

PACKAGE LABEL

MAX STRENGTH MOST POWERFUL DOSE WITHOUT RX

uqora

FOUNDED BY A UTI SUFFERER

UTI PAIN RELIEF

MAX STRENGTH

FAST TARGETED RELIEF FOR

Burning

Pain & discomfort at the source unlike general pain relievers

Urgency

2 Day Supply

12 tablets

99.5 mg Phenazopyridine Hydrochloride

Not intended to replace medical care